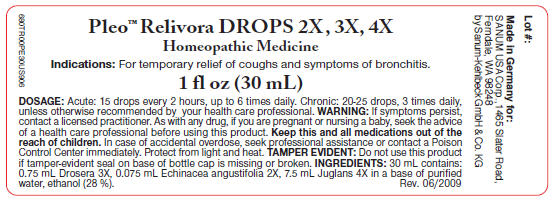 DRUG LABEL: Pleo Relivora
NDC: 60681-6200 | Form: SOLUTION/ DROPS
Manufacturer: Sanum Kehlbeck GmbH & Co. KG
Category: homeopathic | Type: HUMAN OTC DRUG LABEL
Date: 20091130

ACTIVE INGREDIENTS: drosera rotundifolia 3 [hp_X]/30 mL; echinacea angustifolia root 2 [hp_X]/30 mL; english walnut 4 [hp_X]/30 mL
INACTIVE INGREDIENTS: water; alcohol

Pleo™ Relivora
DROPS 2X, 3X, 4X

Homeopathic Medicine

1 fl oz
(30 mL)

Indications

For temporary relief of coughs and symptoms of bronchitis.

INGREDIENTS

30 mL contains 0.75 mL Drosera 3X, 0.075 mL Echinacea angustifolia 2X, 7.5 mL Juglans 4X, water, ethanol (28%).

Tamper Evident

Do not use this product if tamper-evident seal on base of bottle cap is missing or broken or if imprinted security strip on carton is torn.

DOSAGE

Acute

15 drops every two hours, up to 6 times daily.

Chronic

20-25 drops, 3 times daily, unless otherwise recommended by your health care professional.

WARNING

If symptoms persist more than a few days, contact a licensed practitioner. As with any drug, if you are pregnant or nursing a baby, seek the advice of a health care professional before using this product.

KEEP OUT OF REACH OF CHILDREN

Keep this and all other medications out of the reach of children. In case of accidental overdose, seek professional assistance or contact a Poison Control Center immediately.

STORAGE AND HANDLING

Protect from light and heat.

Made in Germany.

Distributed by:
SANUM USA Corp.
1465 Slater Road
Ferndale, WA 98248

Manufactured By:
Sanum-Kehlbeck
GmbH & Co. KG

Rev. 08/2007

PRINCIPAL DISPLAY PANEL - 30 mL Label

Pleo™ Relivora DROPS 2X , 3X, 4X

Homeopathic Medicine

Indications: For temporary relief of coughs and symptoms of bronchitis.

1 fl oz (30 mL)

DOSAGE: Acute: 15 drops every 2 hours, up to 6 times daily. Chronic: 20-25 drops, 3 times daily,
unless otherwise recommended by your health care professional. WARNING: If symptoms persist,
contact a licensed practitioner. As with any drug, if you are pregnant or nursing a baby, seek the advice
of a health care professional before using this product. Keep this and all medications out of the
reach of children. In case of accidental overdose, seek professional assistance or contact a Poison
Control Center immediately. Protect from light and heat. TAMPER EVIDENT: Do not use this product
if tamper-evident seal on base of bottle cap is missing or broken. INGREDIENTS: 30 mL contains:
0.75 mL Drosera 3X, 0.075 mL Echinacea angustifolia 2X, 7.5 mL Juglans 4X in a base of purified
water, ethanol (28 %).
Rev. 06/2009